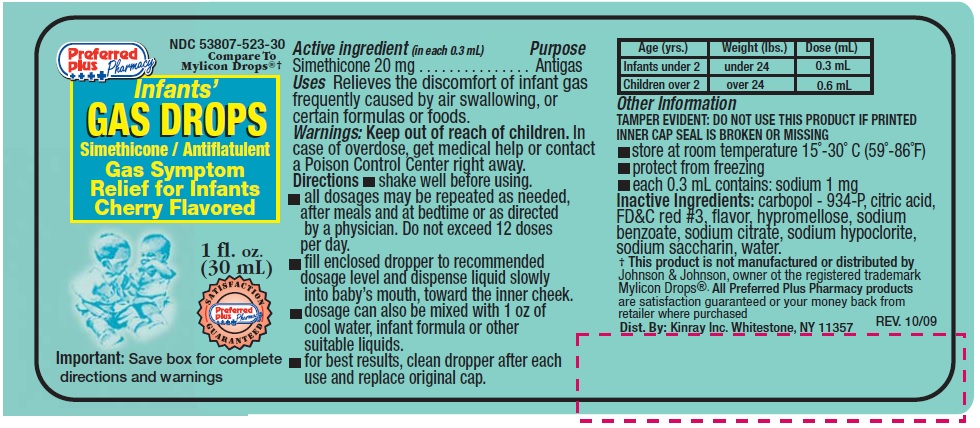 DRUG LABEL: Infants Gas Drops
NDC: 53807-523 | Form: SUSPENSION/ DROPS
Manufacturer: Rij Pharmaceutical Corporation
Category: otc | Type: HUMAN OTC DRUG LABEL
Date: 20180430

ACTIVE INGREDIENTS: Dimethicone 20 mg/0.3 mL
INACTIVE INGREDIENTS: SODIUM; CARBOMER HOMOPOLYMER TYPE B (ALLYL SUCROSE CROSSLINKED); CITRIC ACID MONOHYDRATE; FD&C RED NO. 3; HYPROMELLOSES; SODIUM BENZOATE; SODIUM CITRATE; SODIUM HYPOCHLORITE; SACCHARIN SODIUM; WATER

Drug Facts

Active ingredients (in each 0.3mL)

Simethicone 20 mg

Purpose

Antigas

Uses

Relieves the discomfort of gas frequently caused by air swallowing, or certain formulas or foods.

Warnings

Keep out of reach of children. In case of overdose get medical help or contact a Poison Control Center right away.

Directions

- shake well before using
- all dosages may be repeated as needed, after meals and at bedtime or as directed by a physician. Do not exceed 12 doses per day.
- fill enclosed dropper to recommended dosage level and dispense liquid slowly into baby's mouth, toward the inner cheek
- dosage can also be mixed with 1 oz.of cool water, infant formula or other suitable liquids
- for best results, clean dropper after each use and replace original cap.

Age (yrs) | Weight (lbs) | Dose (ml)
Infants under 2 | Under 24 | 0.3 mL
Children over 2 | Over 24 | 0.6 mL

Other Information

- TAMPER EVIDENT: DO NOT USE THIS PRODUCT IF PRINTED INNER CAP SEAL IS BROKEN OR MISSING
- Store at room temperature 15° - 30°C (59 - 86°F)
- protect from freezing
- each 0.3 mL contains: sodium 1 mg

Inactive ingredients

carbopol - 934-P, citric acid, FD&C red #3, flavor, hypromellose, sodium benzoate, sodium citrate, sodium hypoclorite, sodium saccharin, water